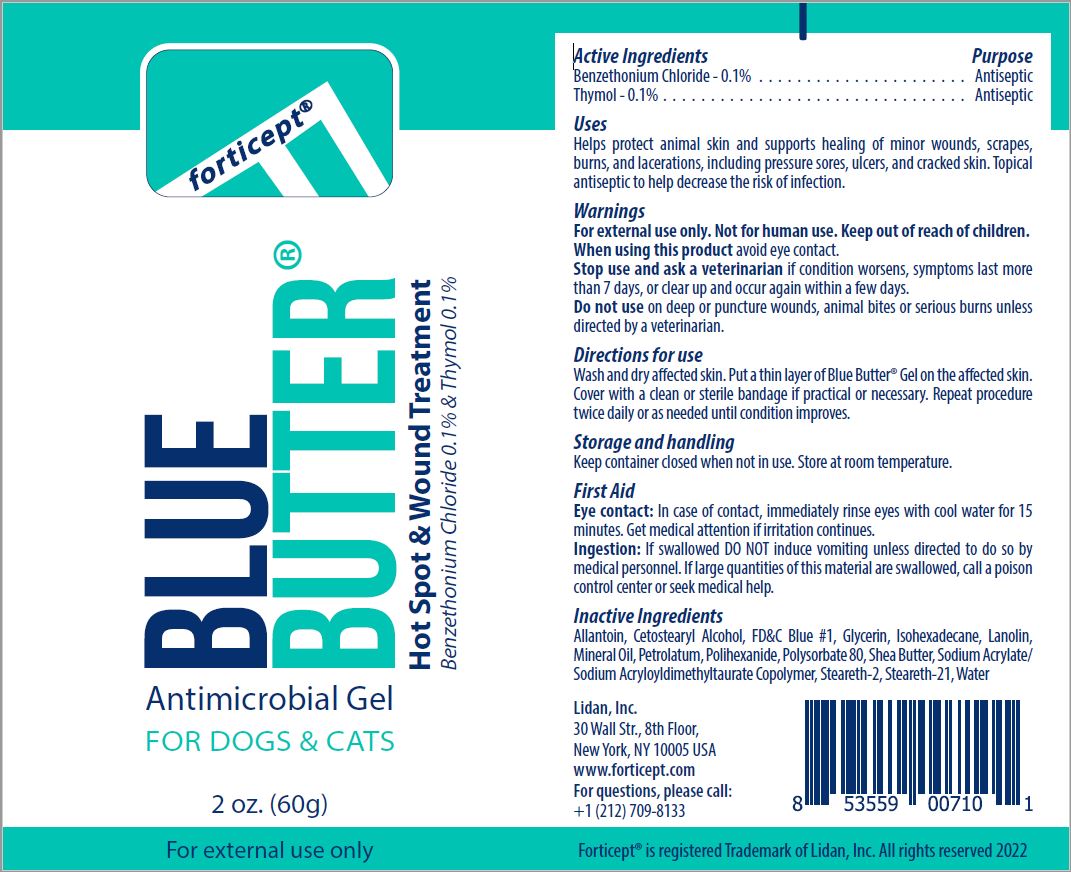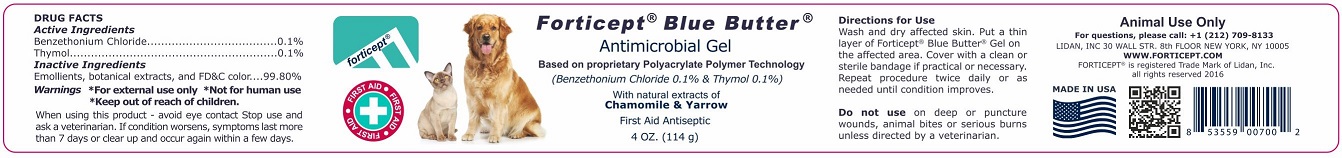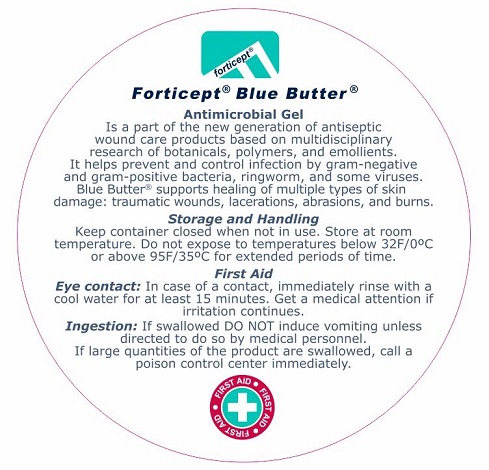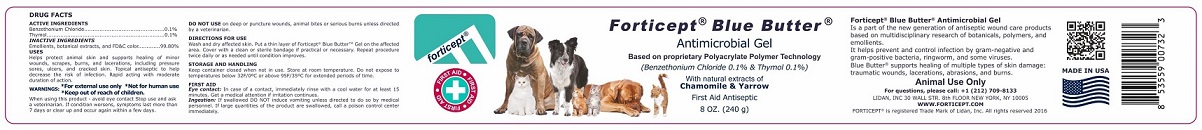 DRUG LABEL: Forticept Blue Butter Antimicrobial Gel
NDC: 72127-0702 | Form: Gel
Manufacturer: Lidan, Inc.
Category: animal | Type: OTC ANIMAL DRUG LABEL
Date: 20230113

ACTIVE INGREDIENTS: benzethonium chloride 1 g/1000 g; thymol 1 g/1000 g

Active Ingredients

Benzethonium Chloride .................................................................0.1%
Thymol .......................................................................................0.1%

Inactive ingredients:

Emollients, botanical extracts, and FD&C colors.............................................................99.8%

Uses

Helps protect animal skin and supports healing of minor wounds, scrapes, burns, and lacerations, including pressure sores, ulcers, and cracked skin. Topical antiseptic to help decrease the risk of infection.

Rapid-acting with moderate duration of action.

Warnings

*For external use only *Not for human use *Keep out of reach of children.

When using this product - avoid eye contact. Stop use and ask a veterinarian: If condition worsens, symptoms last more than 7 days, or clear up and occur again within a few days.

Do not use on deep or puncture wounds, animal bites or serious burns unless directed by a veterinarian.

Directions for use

Wash and dry affected skin. Put a thin layer of Forticept Blue Butter Gel on the affected skin. Cover with a clean or sterile bandage if practical or necessary. Repeat procedure twice daily or as needed until condition improves.

Storage and handling

Keep container closed when not in use. Store at room temperature. Do not expose to temperatures below 32F/0oC or above 95F/35oC for extended periods of time.

FIRST AID

Eye contact: In case of contact, immediately rinse eyes with cool water for 15 minutes. Get medical attention if irritation continues.

Ingestion: If swallowed DO NOT induce vomiting unless directed to do so by medical personnel. If large quantities of this material are swallowed, call a poison control center immediately.